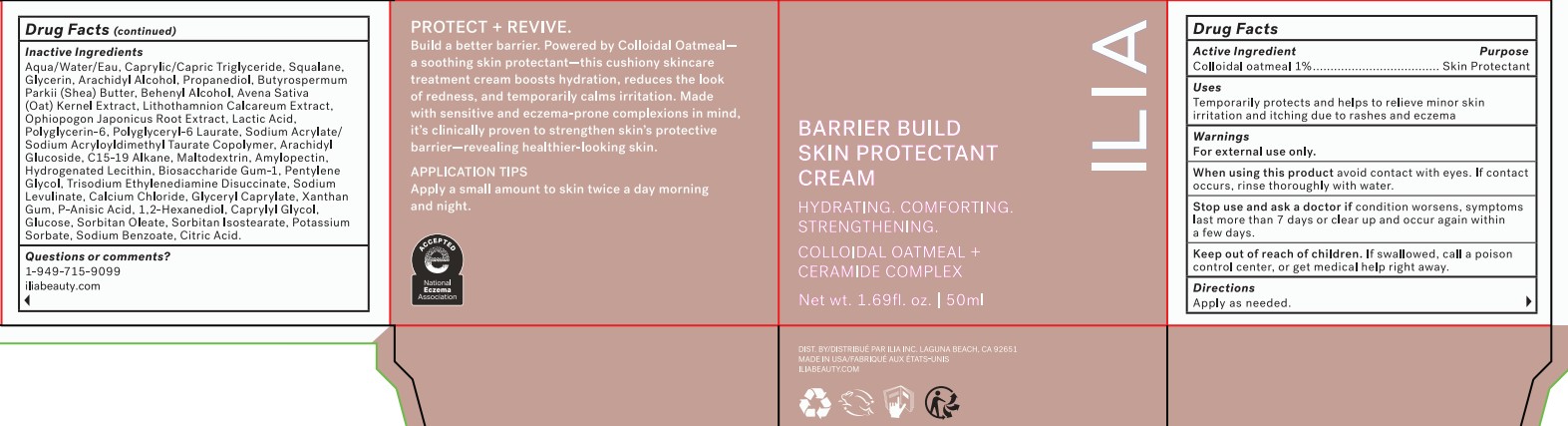 DRUG LABEL: Barrier Build Skin Protectant Cream
NDC: 81110-800 | Form: CREAM
Manufacturer: ILIA, Inc.
Category: otc | Type: HUMAN OTC DRUG LABEL
Date: 20240927

ACTIVE INGREDIENTS: OATMEAL 1 g/100 mL
INACTIVE INGREDIENTS: WATER

Barrier Build Skin Protectant Cream

Active Ingredient

Colloidal Oatmeal 1%

Purpose

Skin Protectant

Uses

Temporarily protects and helps to relieve minor skin irritation and itching due to rashes and eczema

Warnings

For external use only.

When using this product

avoid contact with eyes. If contact occurs, rinse thoroughly with water.

Stop use and ask a doctor if

condition worsens, symptoms last more than 7 days or clear up and occur again within a few days.

Keep out of reach of children.

If swallowed, call a poison control center, or get medical help right away.

Directions

Apply as needed.

Inactive Ingredients:

WATER/AQUA/EAU, CAPRYLIC/CAPRIC TRIGLYCERIDE, SQUALANE, GLYCERIN, ARACHIDYL ALCOHOL, PROPANEDIOL, BUTYROSPERMUM PARKII (SHEA) BUTTER, BEHENYL ALCOHOL, AVENA SATIVA (OAT) KERNEL EXTRACT, SODIUM ACRYLATE/SODIUM ACRYLOYLDIMETHYL TAURATE COPOLYMER, ARACHIDYL GLUCOSIDE, C15-19 ALKANE, 1,2-HEXANEDIOL, CAPRYLYL GLYCOL, OPHIOPOGON JAPONICUS ROOT EXTRACT, PENTYLENE GLYCOL, POLYGLYCERYL-6 LAURATE, MALTODEXTRIN, AMYLOPECTIN, HYDROGENATED LECITHIN, POLYGLYCERIN-6, SORBITAN OLEATE, TRISODIUM ETHYLENEDIAMINE DISUCCINATE, BIOSACCHARIDE GUM-1, LITHOTHAMNION CALCAREUM EXTRACT, SORBITAN ISOSTEARATE, LACTIC ACID, SODIUM LEVULINATE, GLUCOSE, CALCIUM CHLORIDE, GLYCERYL CAPRYLATE, POTASSIUM SORBATE, SODIUM BENZOATE, P-ANISIC ACID, XANTHAN GUM, CITRIC ACID.

Qustions or comments?

1-949-715-9099

iliabeauty.com